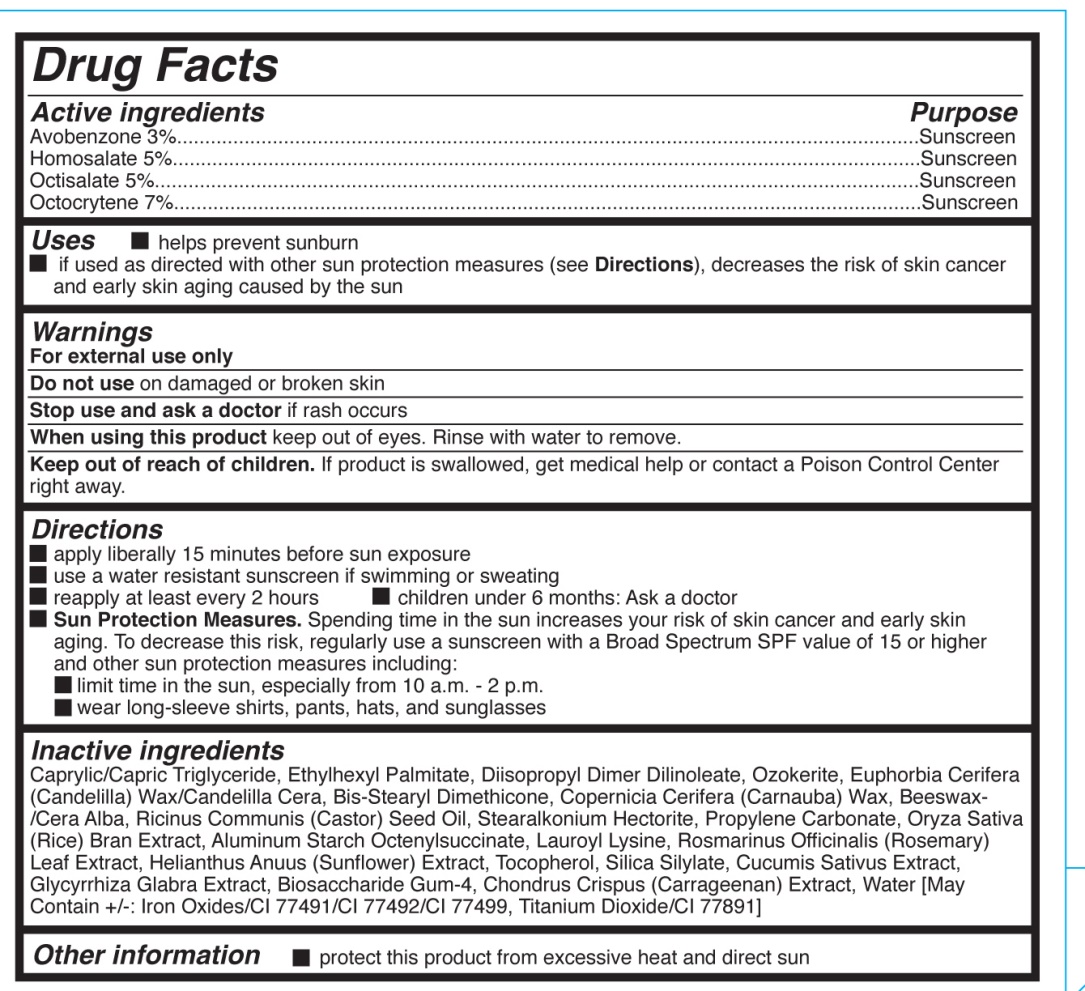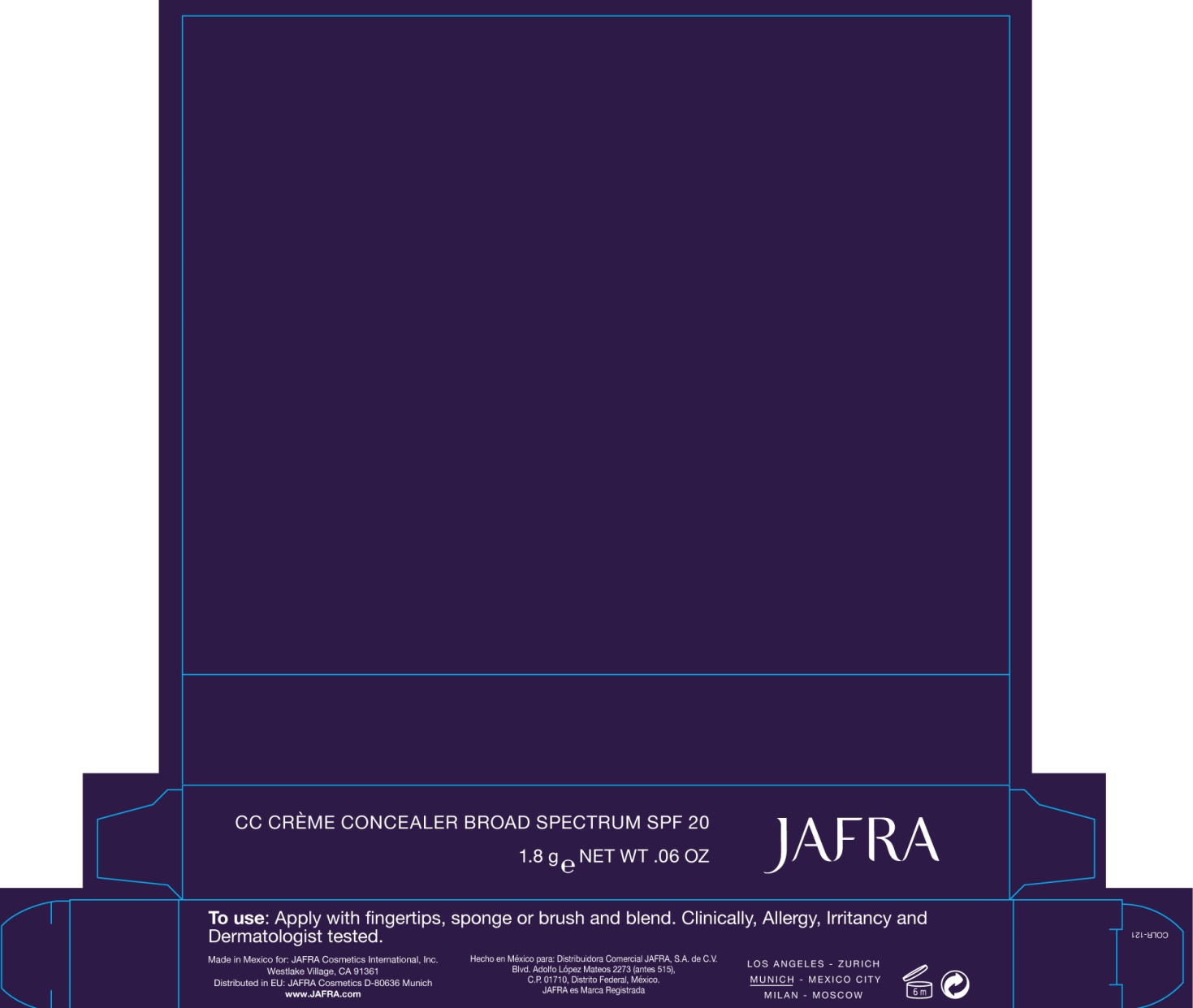 DRUG LABEL: CC Creme Concealer Broad Spectrum SPF 20
NDC: 68828-241 | Form: CREAM
Manufacturer: Jafra Cosmetics International
Category: otc | Type: HUMAN OTC DRUG LABEL
Date: 20190404

ACTIVE INGREDIENTS: AVOBENZONE 3 g/100 g; HOMOSALATE 5 g/100 g; OCTISALATE 5 g/100 g; OCTOCRYLENE 7 g/100 g
INACTIVE INGREDIENTS: MEDIUM-CHAIN TRIGLYCERIDES; ETHYLHEXYL PALMITATE; DIISOPROPYL DILINOLEATE; CERESIN; CANDELILLA WAX; CARNAUBA WAX; WHITE WAX; CASTOR OIL; STEARALKONIUM HECTORITE; PROPYLENE CARBONATE; RICE BRAN; ALUMINUM STARCH OCTENYLSUCCINATE; LAUROYL LYSINE; ROSEMARY; HELIANTHUS ANNUUS FLOWERING TOP; TOCOPHEROL; CUCUMBER; GLYCYRRHIZA GLABRA; BIOSACCHARIDE GUM-4; CHONDRUS CRISPUS CARRAGEENAN; WATER; FERRIC OXIDE RED; FERRIC OXIDE YELLOW; FERROSOFERRIC OXIDE; TITANIUM DIOXIDE

CC Creme Concealer Broad Spectrum SPF 20

Active ingredients Purpose

Avobenzone 3% Sunscreen

Homosalate 5% Sunscreen

Octisalate 5% Sunscreen

Octocrylene 7% Sunscreen

Uses

helps prevent sunburn

if used as directed with other sun protection measures (see Directions), decreases the risk of cancer and early skin aging

Keep out of reach of children. If product is swallowed, get medical help or contact a Poison Control Center right away

Stop use and ask a doctor if rash occurs

warnings

For external use only

Do not use on damaged or broken skin

When using this product keep out of eyes.

Directions

apply liberally 15 minutes before sun exposure

use a water resistant sunscreen if swimming or sweating

reapply at least every 2 hours

Children under 6 months:Ask a doctor

Sun Protection Measures. Spending time in the sun increases your risk of skin cancer and early skin aging. To decrease this risk, regularly use a sunscreen with a Broad Spectrum SPF value of 15 or higher and other sun protection measures including:

Limit time in the sun, especially from 10 a.m. - 2 p.m.

Wear long sleeve shirts, pants, hats, and sunglasses

Inactive ingredients

Caprylic/Capric Triglyceride, Ethylhexyl Palmitate, Diisopropyl Dimer Dilinoleate, Ozokerite, Euphorbia Cerifera (Candelilla) Wax/Candelilla Cera, Bis-Stearyl Dimethicone, Copernicia Cerifera (Carnauba) Wax, Beeswax- /Cera Alba, Ricinus Communis (Castor) Seed Oil, Stearalkonium Hectorite, Propylene Carbonate, Oryza Sativa (Rice) Bran Extract, Aluminum Starch Octenylsuccinate, Lauroyl Lysine, Rosmarinus Officinalis (Rosemary) Leaf Extract, Helianthus Anuus (Sunflower) Extract, Tocopherol, Silica Silylate, Cucumis Sativus Extract, Glycyrrhiza Glabra Extract, Biosaccharide Gum-4, Chondrus Crispus (Carrageenan) Extract, Water [May Contain +/-: Iron Oxides/CI 77491/CI 77492/CI 77499, Titanium Dioxide/CI 77891]

PACKAGE LABEL

CC Creme Concealer Broad Spectrum SPF 20

1.8g Net wt. .06 oz